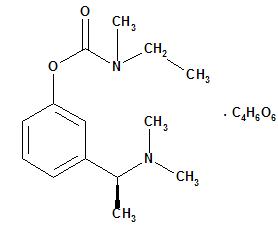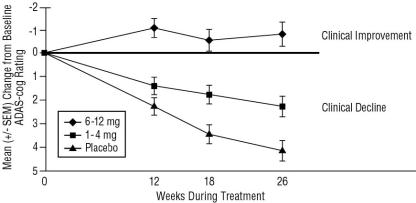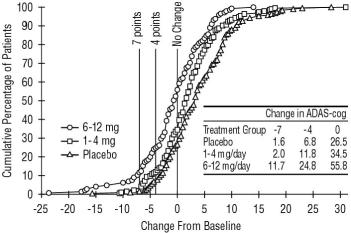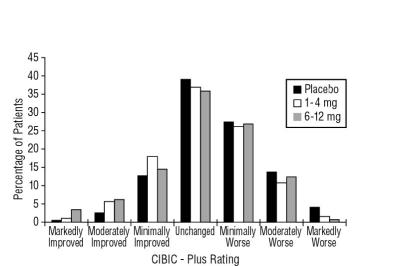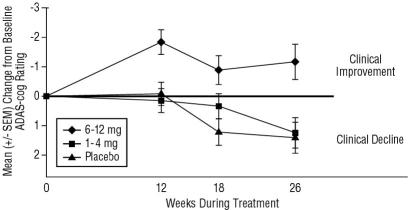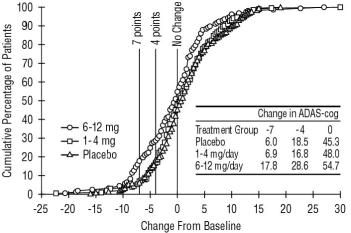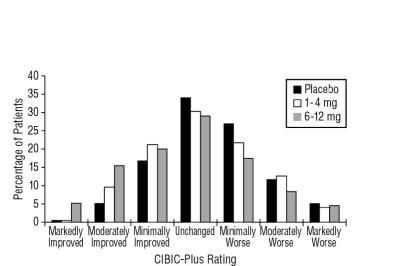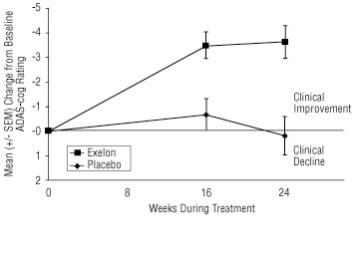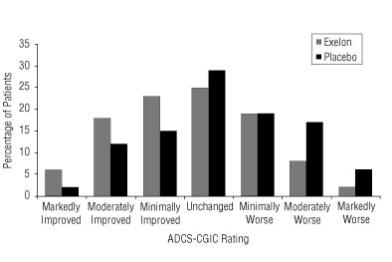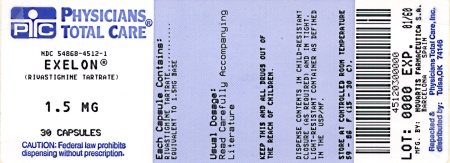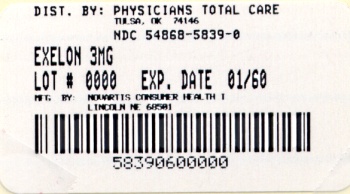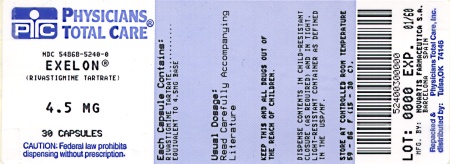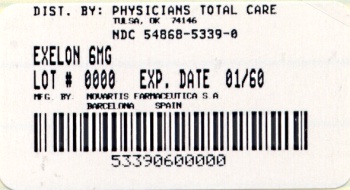 DRUG LABEL: Exelon
NDC: 54868-4512 | Form: CAPSULE
Manufacturer: Physicians Total Care, Inc.
Category: prescription | Type: HUMAN PRESCRIPTION DRUG LABEL
Date: 20100609

ACTIVE INGREDIENTS: RIVASTIGMINE TARTRATE 1.5 mg/1 1
INACTIVE INGREDIENTS: GELATIN; HYPROMELLOSE; MAGNESIUM STEARATE; CELLULOSE, MICROCRYSTALLINE; FERRIC OXIDE RED; SILICON DIOXIDE; TITANIUM DIOXIDE; FERRIC OXIDE YELLOW

T2006-73

Exelon®

(rivastigmine tartrate)

Capsules and Oral Solution

Rx only

Prescribing Information

DESCRIPTION

Exelon® (rivastigmine tartrate) is a reversible cholinesterase inhibitor and is known chemically as (S)-N-Ethyl-N-methyl-3-[1-(dimethylamino)ethyl]-phenyl carbamate hydrogen-(2R,3R)-tartrate. Rivastigmine tartrate is commonly referred to in the pharmacological literature as SDZ ENA 713 or ENA 713. It has an empirical formula of C14H22N2O2 • C4H6O6 (hydrogen tartrate salt – hta salt) and a molecular weight of 400.43 (hta salt). Rivastigmine tartrate is a white to off-white, fine crystalline powder that is very soluble in water, soluble in ethanol and acetonitrile, slightly soluble in n-octanol and very slightly soluble in ethyl acetate. The distribution coefficient at 37°C in n-octanol/phosphate buffer solution pH 7 is 3.0.

Exelon Capsules contain rivastigmine tartrate, equivalent to 1.5, 3, 4.5 and 6 mg of rivastigmine base for oral administration. Inactive ingredients are hydroxypropyl methylcellulose, magnesium stearate, microcrystalline cellulose, and silicon dioxide. Each hard-gelatin capsule contains gelatin, titanium dioxide and red and/or yellow iron oxides.

Exelon Oral Solution is supplied as a solution containing rivastigmine tartrate, equivalent to 2 mg/mL of rivastigmine base for oral administration. Inactive ingredients are citric acid, D&C yellow #10, purified water, sodium benzoate and sodium citrate.

CLINICAL PHARMACOLOGY

Mechanism of Action

Pathological changes in dementia of the Alzheimer’s type and dementia associated with Parkinson’s disease involve cholinergic neuronal pathways that project from the basal forebrain to the cerebral cortex and hippocampus. These pathways are thought to be intricately involved in memory, attention, learning, and other cognitive processes. While the precise mechanism of rivastigmine's action is unknown, it is postulated to exert its therapeutic effect by enhancing cholinergic function. This is accomplished by increasing the concentration of acetylcholine through reversible inhibition of its hydrolysis by cholinesterase. If this proposed mechanism is correct, Exelon's effect may lessen as the disease process advances and fewer cholinergic neurons remain functionally intact. There is no evidence that rivastigmine alters the course of the underlying dementing process. After a 6-mg dose of rivastigmine, anticholinesterase activity is present in CSF for about 10 hours, with a maximum inhibition of about 60% 5 hours after dosing.

In vitro and in vivo studies demonstrate that the inhibition of cholinesterase by rivastigmine is not affected by the concomitant administration of memantine, an N-methyl-D-aspartate receptor antagonist.

Clinical Trial Data Dementia of the Alzheimer’s Type

The effectiveness of Exelon® (rivastigmine tartrate) as a treatment for Alzheimer's disease is demonstrated by the results of 2 randomized, double-blind, placebo-controlled clinical investigations in patients with Alzheimer's disease [diagnosed by NINCDS-ADRDA and DSM-IV criteria, Mini-Mental State Examination (MMSE) greater than or equal to 10 and less than or equal to 26, and the Global Deterioration Scale (GDS)]. The mean age of patients participating in Exelon trials was 73 years with a range of 41-95. Approximately 59% of patients were women and 41% were men. The racial distribution was Caucasian 87%, Black 4% and other races 9%.

Study Outcome Measures

In each study, the effectiveness of Exelon was evaluated using a dual outcome assessment strategy.

The ability of Exelon to improve cognitive performance was assessed with the cognitive subscale of the Alzheimer's Disease Assessment Scale (ADAS-cog), a multi-item instrument that has been extensively validated in longitudinal cohorts of Alzheimer's disease patients. The ADAS-cog examines selected aspects of cognitive performance including elements of memory, orientation, attention, reasoning, language and praxis. The ADAS-cog scoring range is from 0 to 70, with higher scores indicating greater cognitive impairment. Elderly normal adults may score as low as 0 or 1, but it is not unusual for non-demented adults to score slightly higher.

The patients recruited as participants in each study had mean scores on ADAS-cog of approximately 23 units, with a range from 1 to 61. Experience gained in longitudinal studies of ambulatory patients with mild to moderate Alzheimer's disease suggests that they gain 6-12 units a year on the ADAS-cog. Lesser degrees of change, however, are seen in patients with very mild or very advanced disease because the ADAS-cog is not uniformly sensitive to change over the course of the disease. The annualized rate of decline in the placebo patients participating in Exelon trials was approximately 3-8 units per year.

The ability of Exelon to produce an overall clinical effect was assessed using a Clinician's Interview-Based Impression of Change (CIBIC) that required the use of caregiver information, the CIBIC-Plus. The CIBIC-Plus is not a single instrument and is not a standardized instrument like the ADAS-cog. Clinical trials for investigational drugs have used a variety of CIBIC formats, each different in terms of depth and structure. As such, results from a CIBIC-Plus reflect clinical experience from the trial or trials in which it was used and cannot be compared directly with the results of CIBIC-Plus evaluations from other clinical trials. The CIBIC-Plus used in the Exelon trials was a structured instrument based on a comprehensive evaluation at baseline and subsequent time-points of three domains: patient cognition, behavior and functioning, including assessment of activities of daily living. It represents the assessment of a skilled clinician using validated scales based on his/her observation at interviews conducted separately with the patient and the caregiver familiar with the behavior of the patient over the interval rated. The CIBIC-Plus is scored as a 7-point categorical rating, ranging from a score of 1, indicating "markedly improved," to a score of 4, indicating "no change" to a score of 7, indicating "marked worsening." The CIBIC-Plus has not been systematically compared directly to assessments not using information from caregivers or other global methods.

U.S. 26-Week Study

In a study of 26 weeks duration, 699 patients were randomized to either a dose range of 1-4 mg or 6-12 mg of Exelon per day or to placebo, each given in divided doses. The 26-week study was divided into a 12-week forced-dose titration phase and a 14-week maintenance phase. The patients in the active treatment arms of the study were maintained at their highest tolerated dose within the respective range.

Effects on the ADAS-cog: Figure 1 illustrates the time course for the change from baseline in ADAS-cog scores for all three dose groups over the 26 weeks of the study. At 26 weeks of treatment, the mean differences in the ADAS-cog change scores for the Exelon-treated patients compared to the patients on placebo were 1.9 and 4.9 units for the 1-4 mg and 6-12 mg treatments, respectively. Both treatments were statistically significantly superior to placebo and the 6-12 mg/day range was significantly superior to the 1-4 mg/day range.

Figure 1: Time-course of the Change from Baseline in ADAS-cog Score for Patients Completing 26 Weeks of Treatment

Figure 2 illustrates the cumulative percentages of patients from each of the three treatment groups who had attained at least the measure of improvement in ADAS-cog score shown on the X axis. Three change scores, (7-point and 4-point reductions from baseline or no change in score) have been identified for illustrative purposes, and the percent of patients in each group achieving that result is shown in the inset table.

The curves demonstrate that both patients assigned to Exelon and placebo have a wide range of responses, but that the Exelon groups are more likely to show the greater improvements. A curve for an effective treatment would be shifted to the left of the curve for placebo, while an ineffective or deleterious treatment would be superimposed upon, or shifted to the right of the curve for placebo, respectively.

Figure 2: Cumulative Percentage of Patients Completing 26 Weeks of Double-blind Treatment with Specified Changes from Baseline ADAS-cog Scores. The Percentages of Randomized Patients who Completed the Study were: Placebo 84%, 1-4 mg 85%, and 6-12 mg 65%.

Effects on the CIBIC-Plus: Figure 3 is a histogram of the frequency distribution of CIBIC-Plus scores attained by patients assigned to each of the three treatment groups who completed 26 weeks of treatment. The mean Exelon-placebo differences for these groups of patients in the mean rating of change from baseline were 0.32 units and 0.35 units for 1-4 mg and 6-12 mg of Exelon, respectively. The mean ratings for the 6-12 mg/day and 1-4 mg/day groups were statistically significantly superior to placebo. The differences between the 6-12 mg/day and the 1-4 mg/day groups were statistically significant.

Figure 3: Frequency Distribution of CIBIC-Plus Scores at Week 26

Global 26-Week Study

In a second study of 26 weeks duration, 725 patients were randomized to either a dose range of 1-4 mg or 6-12 mg of Exelon per day or to placebo, each given in divided doses. The 26-week study was divided into a 12-week forced-dose titration phase and a 14-week maintenance phase. The patients in the active treatment arms of the study were maintained at their highest tolerated dose within the respective range.

Effects on the ADAS-cog: Figure 4 illustrates the time course for the change from baseline in ADAS-cog scores for all three dose groups over the 26 weeks of the study. At 26 weeks of treatment, the mean differences in the ADAS-cog change scores for the Exelon-treated patients compared to the patients on placebo were 0.2 and 2.6 units for the 1-4 mg and 6-12 mg treatments, respectively. The 6-12 mg/day group was statistically significantly superior to placebo, as well as to the 1-4 mg/day group. The difference between the 1-4 mg/day group and placebo was not statistically significant.

Figure 4: Time-course of the Change from Baseline in ADAS-cog Score for Patients Completing 26 Weeks of Treatment

Figure 5 illustrates the cumulative percentages of patients from each of the three treatment groups who had attained at least the measure of improvement in ADAS-cog score shown on the X axis. Similar to the U.S. 26-week study, the curves demonstrate that both patients assigned to Exelon and placebo have a wide range of responses, but that the 6-12 mg/day Exelon group is more likely to show the greater improvements.

Figure 5: Cumulative Percentage of Patients Completing 26 Weeks of Double-blind Treatment with Specified Changes from Baseline ADAS-cog Scores. The Percentages of Randomized Patients who Completed the Study were: Placebo 87%, 1-4 mg 86%, and 6-12 mg 67%.

Effects on the CIBIC-Plus: Figure 6 is a histogram of the frequency distribution of CIBIC-Plus scores attained by patients assigned to each of the three treatment groups who completed 26 weeks of treatment. The mean Exelon-placebo differences for these groups of patients for the mean rating of change from baseline were 0.14 units and 0.41 units for 1-4 mg and 6-12 mg of Exelon, respectively. The mean ratings for the 6-12 mg/day group were statistically significantly superior to placebo. The comparison of the mean ratings for the 1-4 mg/day group and placebo group was not statistically significant.

Figure 6: Frequency Distribution of CIBIC-Plus Scores at Week 26

U.S. Fixed-Dose Study

In a study of 26 weeks duration, 702 patients were randomized to doses of 3, 6, or 9 mg/day of Exelon or to placebo, each given in divided doses. The fixed-dose study design, which included a 12-week forced-dose titration phase and a 14-week maintenance phase, led to a high dropout rate in the 9 mg/day group because of poor tolerability. At 26 weeks of treatment, significant differences were observed for the ADAS-cog mean change from baseline for the 9 mg/day and 6 mg/day groups, compared to placebo. No significant differences were observed between any of the Exelon-dose groups and placebo for the analysis of the CIBIC-Plus mean rating of change. Although no significant differences were observed between Exelon treatment groups, there was a trend toward numerical superiority with higher doses.

Dementia Associated with Parkinson’s Disease (PDD) International 24-Week Study

The effectiveness of Exelon as a treatment for dementia associated with Parkinson’s disease is demonstrated by the results of one randomized, double-blind, placebo-controlled clinical investigation in patients with mild to moderate dementia, with onset at least 2 years after the initial diagnosis of idiopathic Parkinson’s disease. The diagnosis of idiopathic Parkinson’s disease was based on the United Kingdom Parkinson’s Disease Society Brain Bank clinical criteria. The diagnosis of dementia was based on the criteria stipulated under the DSM-IV category “Dementia Due To Other General Medical Condition” (code 294.1x), but patients were not required to have a distinctive pattern of cognitive deficits as part of the dementia. Alternate causes of dementia were excluded by clinical history, physical and neurological examination, brain imaging, and relevant blood tests. Patients enrolled in the study had a MMSE score greater than or equal to 10 and less than or equal to 24 at entry. The mean age of patients participating in this trial was 72.7 years with a range of 50–91. Approximately, 35.1% of patients were women and 64.9% of patients were men. The racial distribution was 99.6% Caucasian and other races 0.4%.

Study Outcome Measures

This study used a dual outcome assessment strategy to evaluate the effectiveness of Exelon.

The ability of Exelon to improve cognitive performance was assessed with the ADAS-cog.

The ability of Exelon to produce an overall clinical effect was assessed using the Alzheimer’s Disease Cooperative Study – Clinician’s Global Impression of Change (ADCS-CGIC). The ADCS-CGIC is a more standardized form of CIBIC-Plus and is also scored as a 7-point categorical rating, ranging from a score of 1, indicating "markedly improved," to a score of 4, indicating "no change" to a score of 7, indicating "marked worsening."

Study Results

In this study, 541 patients were randomized to a dose range of 3–12 mg of Exelon per day or to placebo in a ratio of 2:1, given in divided doses. The 24-week study was divided into a 16-week titration phase and an 8-week maintenance phase. The patients in the active treatment arm of the study were maintained at their highest tolerated dose within the specified dose range.

Effects on the ADAS-cog: Figure 7 illustrates the time course for the change from baseline in ADAS-cog scores for both treatment groups over the 24-week study. At 24 weeks of treatment, the mean difference in the ADAS-cog change scores for the Exelon-treated patients compared to the patients on placebo was 3.8 points. This treatment difference was statistically significant in favor of Exelon when compared to placebo.

Figure 7:Time Course of the Change from Baseline in ADAS-cog Score for Patients Completing 24 Weeks of Treatment

Effects on the ADCS-CGIC: Figure 8 is a histogram of the distribution of patients’ scores on the ADCS-CGIC (Alzheimer’s Disease Cooperative Study - Clinician’s Global Impression of Change) at 24 weeks. The mean difference in change scores between the Exelon and placebo groups from baseline was 0.5 points. This difference was statistically significant in favor of Exelon treatment.

Figure 8:Distribution of ADCS-CGIC Scores for Patients Completing 24 Weeks of Treatment

Age, Gender and Race

Patients’ age, gender, or race did not predict clinical outcome of Exelon treatment.

Pharmacokinetics

Rivastigmine is well absorbed with absolute bioavailability of about 40% (3-mg dose). It shows linear pharmacokinetics up to 3 mg BID but is non-linear at higher doses. Doubling the dose from 3 to 6 mg BID results in a 3-fold increase in AUC. The elimination half-life is about 1.5 hours, with most elimination as metabolites via the urine.

Absorption: Rivastigmine is rapidly and completely absorbed. Peak plasma concentrations are reached in approximately 1 hour. Absolute bioavailability after a 3-mg dose is about 36%. Administration of Exelon with food delays absorption (tmax) by 90 minutes, lowers Cmax by approximately 30% and increases AUC by approximately 30%.

Distribution: Rivastigmine is widely distributed throughout the body with a volume of distribution in the range of 1.8-2.7 L/kg. Rivastigmine penetrates the blood brain barrier, reaching CSF peak concentrations in 1.4-2.6 hours. Mean AUC1-12hr ratio of CSF/plasma averaged 40 ± 0.5% following 1-6 mg BID doses.

Rivastigmine is about 40% bound to plasma proteins at concentrations of 1-400 ng/mL, which cover the therapeutic concentration range. Rivastigmine distributes equally between blood and plasma with a blood-to-plasma partition ratio of 0.9 at concentrations ranging from 1-400 ng/mL.

Metabolism: Rivastigmine is rapidly and extensively metabolized, primarily via cholinesterase-mediated hydrolysis to the decarbamylated metabolite. Based on evidence from in vitro and animal studies, the major cytochrome P450 isozymes are minimally involved in rivastigmine metabolism. Consistent with these observations is the finding that no drug interactions related to cytochrome P450 have been observed in humans (see Drug-Drug Interactions).

Elimination: The major pathway of elimination is via the kidneys. Following administration of ^14C-rivastigmine to 6 healthy volunteers, total recovery of radioactivity over 120 hours was 97% in urine and 0.4% in feces. No parent drug was detected in urine. The sulfate conjugate of the decarbamylated metabolite is the major component excreted in urine and represents 40% of the dose. Mean oral clearance of rivastigmine is 1.8 ± 0.6 L/min after 6 mg BID.

Special Populations

Hepatic Disease: Following a single 3-mg dose, mean oral clearance of rivastigmine was 60% lower in hepatically impaired patients (n=10, biopsy proven) than in healthy subjects (n=10). After multiple 6-mg BID oral dosing, the mean clearance of rivastigmine was 65% lower in mild (n=7, Child-Pugh score 5-6) and moderate (n=3, Child-Pugh score 7-9) hepatically impaired patients (biopsy proven, liver cirrhosis) than in healthy subjects (n=10). Dosage adjustment is not necessary in hepatically impaired patients as the dose of drug is individually titrated to tolerability.

Renal Disease: Following a single 3-mg dose, mean oral clearance of rivastigmine is 64% lower in moderately impaired renal patients (n=8, GFR=10-50 mL/min) than in healthy subjects (n=10, GFR greater than or equal to 60 mL/min); Cl/F=1.7 L/min (cv=45%) and 4.8 L/min (cv=80%), respectively. In severely impaired renal patients (n=8, GFR less than 10 mL/min), mean oral clearance of rivastigmine is 43% higher than in healthy subjects (n=10, GFR greater than or equal to 60 mL/min); Cl/F=6.9 L/min and 4.8 L/min, respectively. For unexplained reasons, the severely impaired renal patients had a higher clearance of rivastigmine than moderately impaired patients. However, dosage adjustment may not be necessary in renally impaired patients as the dose of the drug is individually titrated to tolerability.

Age: Following a single 2.5-mg oral dose to elderly volunteers (greater than 60 years of age, n=24) and younger volunteers (n=24), mean oral clearance of rivastigmine was 30% lower in elderly (7 L/min) than in younger subjects (10 L/min).

Gender and Race: No specific pharmacokinetic study was conducted to investigate the effect of gender and race on the disposition of Exelon, but a population pharmacokinetic analysis indicates that gender (n=277 males and 348 females) and race (n=575 White, 34 Black, 4 Asian, and 12 Other) did not affect the clearance of Exelon.

Nicotine Use: Population PK analysis showed that nicotine use increases the oral clearance of rivastigmine by 23% (n=75 Smokers and 549 Nonsmokers).

Drug-Drug Interactions

Effect of Exelon on the Metabolism of Other Drugs: Rivastigmine is primarily metabolized through hydrolysis by esterases. Minimal metabolism occurs via the major cytochrome P450 isoenzymes. Based on in vitro studies, no pharmacokinetic drug interactions with drugs metabolized by the following isoenzyme systems are expected: CYP1A2, CYP2D6, CYP3A4/5, CYP2E1, CYP2C9, CYP2C8, or CYP2C19.

No pharmacokinetic interaction was observed between rivastigmine and digoxin, warfarin, diazepam, or fluoxetine in studies in healthy volunteers. The elevation of prothrombin time induced by warfarin is not affected by administration of Exelon.

Effect of Other Drugs on the Metabolism of Exelon: Drugs that induce or inhibit CYP450 metabolism are not expected to alter the metabolism of rivastigmine. Single-dose pharmacokinetic studies demonstrated that the metabolism of rivastigmine is not significantly affected by concurrent administration of digoxin, warfarin, diazepam, or fluoxetine.

Population PK analysis with a database of 625 patients showed that the pharmacokinetics of rivastigmine were not influenced by commonly prescribed medications such as antacids (n=77), antihypertensives (n=72), ß-blockers (n=42), calcium channel blockers (n=75), antidiabetics (n=21), nonsteroidal antiinflammatory drugs (n=79), estrogens (n=70), salicylate analgesics (n=177), antianginals (n=35), and antihistamines (n=15). In addition, in clinical trials, no increased risk of clinically relevant untoward effects was observed in patients treated concomitantly with Exelon and these agents.

INDICATIONS AND USAGE

Exelon® (rivastigmine tartrate) is indicated for the treatment of mild to moderate dementia of the Alzheimer's type.

Exelon® (rivastigmine tartrate) is indicated for the treatment of mild to moderate dementia associated with Parkinson’s disease.

The dementia of Parkinson’s disease is purportedly characterized by impairments in executive function, memory retrieval, and attention in patients with an established diagnosis of Parkinson’s disease. The diagnosis of the dementia of Parkinson’s disease, however, can reliably be made in patients in whom a progressive dementia syndrome occurs (without the necessity to document the specific deficits described above) at least 2 years after a diagnosis of Parkinson’s disease has been made, and in whom other causes of dementia have been ruled out (see CLINICAL PHARMACOLOGY, Clinical Trial Data).

CONTRAINDICATIONS

Exelon® (rivastigmine tartrate) is contraindicated in patients with known hypersensitivity to rivastigmine, other carbamate derivatives or other components of the formulation (see DESCRIPTION).

WARNINGS

Gastrointestinal Adverse Reactions

Exelon® (rivastigmine tartrate) use is associated with significant gastrointestinal adverse reactions, including nausea and vomiting, anorexia, and weight loss. For this reason, patients should always be started at a dose of 1.5 mg BID and titrated to their maintenance dose. If treatment is interrupted for longer than several days, treatment should be reinitiated with the lowest daily dose (see DOSAGE AND ADMINISTRATION) to reduce the possibility of severe vomiting and its potentially serious sequelae (e.g., there has been one postmarketing report of severe vomiting with esophageal rupture following inappropriate reinitiation of treatment with a 4.5-mg dose after 8 weeks of treatment interruption).

Nausea and Vomiting: In the controlled clinical trials, 47% of the patients treated with an Exelon dose in the therapeutic range of 6-12 mg/day (n=1189) developed nausea (compared with 12% in placebo). A total of 31% of Exelon-treated patients developed at least one episode of vomiting (compared with 6% for placebo). The rate of vomiting was higher during the titration phase (24% vs. 3% for placebo) than in the maintenance phase (14% vs. 3% for placebo). The rates were higher in women than men. Five percent of patients discontinued for vomiting, compared to less than 1% for patients on placebo. Vomiting was severe in 2% of Exelon-treated patients and was rated as mild or moderate each in 14% of patients. The rate of nausea was higher during the titration phase (43% vs. 9% for placebo) than in the maintenance phase (17% vs. 4% for placebo).

Weight Loss: In the controlled trials, approximately 26% of women on high doses of Exelon (greater than 9 mg/day) had weight loss equal to or greater than 7% of their baseline weight compared to 6% in the placebo-treated patients. About 18% of the males in the high-dose group experienced a similar degree of weight loss compared to 4% in placebo-treated patients. It is not clear how much of the weight loss was associated with anorexia, nausea, vomiting, and the diarrhea associated with the drug.

Anorexia: In the controlled clinical trials, of the patients treated with an Exelon dose of 6-12 mg/day, 17% developed anorexia compared to 3% of the placebo patients. Neither the time course nor the severity of the anorexia is known.

Peptic Ulcers/Gastrointestinal Bleeding: Because of their pharmacological action, cholinesterase inhibitors may be expected to increase gastric acid secretion due to increased cholinergic activity. Therefore, patients should be monitored closely for symptoms of active or occult gastrointestinal bleeding, especially those at increased risk for developing ulcers, e.g., those with a history of ulcer disease or those receiving concurrent nonsteroidal antiinflammatory drugs (NSAIDs). Clinical studies of Exelon have shown no significant increase, relative to placebo, in the incidence of either peptic ulcer disease or gastrointestinal bleeding.

Anesthesia

Exelon as a cholinesterase inhibitor, is likely to exaggerate succinylcholine-type muscle relaxation during anesthesia.

Cardiovascular Conditions

Drugs that increase cholinergic activity may have vagotonic effects on heart rate (e.g., bradycardia). The potential for this action may be particularly important to patients with "sick sinus syndrome" or other supraventricular cardiac conduction conditions. In clinical trials, Exelon was not associated with any increased incidence of cardiovascular adverse events, heart rate or blood pressure changes, or ECG abnormalities. Syncopal episodes have been reported in 3% of patients receiving 6-12 mg/day of Exelon, compared to 2% of placebo patients.

Genitourinary

Although this was not observed in clinical trials of Exelon, drugs that increase cholinergic activity may cause urinary obstruction.

Neurological Conditions

Seizures: Drugs that increase cholinergic activity are believed to have some potential for causing seizures. However, seizure activity also may be a manifestation of Alzheimer's disease.

Pulmonary Conditions

Like other drugs that increase cholinergic activity, Exelon should be used with care in patients with a history of asthma or obstructive pulmonary disease.

PRECAUTIONS

Information for Patients and Caregivers

Caregivers should be advised of the high incidence of nausea and vomiting associated with the use of the drug along with the possibility of anorexia and weight loss. Caregivers should be encouraged to monitor for these adverse events and inform the physician if they occur. It is critical to inform caregivers that if therapy has been interrupted for more than several days, the next dose should not be administered until they have discussed this with the physician.

Caregivers should be instructed in the correct procedure for administering Exelon® (rivastigmine tartrate) Oral Solution. In addition, they should be informed of the existence of an Instruction Sheet (included with the product) describing how the solution is to be administered. They should be urged to read this sheet prior to administering Exelon Oral Solution. Caregivers should direct questions about the administration of the solution to either their physician or pharmacist.

Caregivers and patients should be advised that like other cholinomimetics, Exelon® may exacerbate or induce extrapyramidal symptoms. Worsening in patients with Parkinson’s disease, including an increased incidence or intensity of tremor, has been observed.

Drug-Drug Interactions

Effect of Exelon on the Metabolism of Other Drugs: Rivastigmine is primarily metabolized through hydrolysis by esterases. Minimal metabolism occurs via the major cytochrome P450 isoenzymes. Based on in vitro studies, no pharmacokinetic drug interactions with drugs metabolized by the following isoenzyme systems are expected: CYP1A2, CYP2D6, CYP3A4/5, CYP2E1, CYP2C9, CYP2C8, or CYP2C19.

No pharmacokinetic interaction was observed between rivastigmine and digoxin, warfarin, diazepam, or fluoxetine in studies in healthy volunteers. The elevation of prothrombin time induced by warfarin is not affected by administration of Exelon.

Effect of Other Drugs on the Metabolism of Exelon: Drugs that induce or inhibit CYP450 metabolism are not expected to alter the metabolism of rivastigmine. Single-dose pharmacokinetic studies demonstrated that the metabolism of rivastigmine is not significantly affected by concurrent administration of digoxin, warfarin, diazepam, or fluoxetine.

Population PK analysis with a database of 625 patients showed that the pharmacokinetics of rivastigmine were not influenced by commonly prescribed medications such as antacids (n=77), antihypertensives (n=72), ß-blockers (n=42), calcium channel blockers (n=75), antidiabetics (n=21), nonsteroidal antiinflammatory drugs (n=79), estrogens (n=70), salicylate analgesics (n=177), antianginals (n=35), and antihistamines (n=15).

Use with Anticholinergics: Because of their mechanism of action, cholinesterase inhibitors have the potential to interfere with the activity of anticholinergic medications.

Use with Cholinomimetics and Other Cholinesterase Inhibitors: A synergistic effect may be expected when cholinesterase inhibitors are given concurrently with succinylcholine, similar neuromuscular blocking agents or cholinergic agonists such as bethanechol.

Carcinogenesis, Mutagenesis, Impairment of Fertility

In carcinogenicity studies conducted at dose levels up to 1.1 mg-base/kg/day in rats and 1.6 mg-base/kg/day in mice, rivastigmine was not carcinogenic. These dose levels are approximately 0.9 times and 0.7 times the maximum recommended human daily dose of 12 mg/day on a mg/m^2 basis.

Rivastigmine was clastogenic in two in vitro assays in the presence, but not the absence, of metabolic activation. It caused structural chromosomal aberrations in V79 Chinese hamster lung cells and both structural and numerical (polyploidy) chromosomal aberrations in human peripheral blood lymphocytes. Rivastigmine was not genotoxic in three in vitro assays: the Ames test, the unscheduled DNA synthesis (UDS) test in rat hepatocytes (a test for induction of DNA repair synthesis), and the HGPRT test in V79 Chinese hamster cells. Rivastigmine was not clastogenic in the in vivo mouse micronucleus test.

Rivastigmine had no effect on fertility or reproductive performance in the rat at dose levels up to 1.1 mg-base/kg/day. This dose is approximately 0.9 times the maximum recommended human daily dose of 12 mg/day on a mg/m^2 basis.

Pregnancy

Pregnancy Category B: Reproduction studies conducted in pregnant rats at doses up to 2.3 mg-base/kg/day (approximately 2 times the maximum recommended human dose on a mg/m^2 basis) and in pregnant rabbits at doses up to 2.3 mg-base/kg/day (approximately 4 times the maximum recommended human dose on a mg/m^2 basis) revealed no evidence of teratogenicity. Studies in rats showed slightly decreased fetal/pup weights, usually at doses causing some maternal toxicity; decreased weights were seen at doses which were several fold lower than the maximum recommended human dose on a mg/m^2 basis. There are no adequate or well-controlled studies in pregnant women. Because animal reproduction studies are not always predictive of human response, Exelon should be used during pregnancy only if the potential benefit justifies the potential risk to the fetus.

Nursing Mothers

It is not known whether rivastigmine is excreted in human breast milk. Exelon has no indication for use in nursing mothers.

Pediatric Use

There are no adequate and well-controlled trials documenting the safety and efficacy of Exelon in any illness occurring in children.

ADVERSE REACTIONS

Dementia of the Alzheimer’s Type Adverse Events Leading to Discontinuation

The rate of discontinuation due to adverse events in controlled clinical trials of Exelon® (rivastigmine tartrate) was 15% for patients receiving 6-12 mg/day compared to 5% for patients on placebo during forced weekly dose titration. While on a maintenance dose, the rates were 6% for patients on Exelon compared to 4% for those on placebo.

The most common adverse events leading to discontinuation, defined as those occurring in at least 2% of patients and at twice the incidence seen in placebo patients, are shown in Table 1.

Table 1. Most Frequent Adverse Events Leading to Withdrawal from Clinical Trials during Titration and Maintenance in Patients Receiving 6-12 mg/day Exelon® Using a Forced-Dose Titration
Study Phase | Titration | Maintenance | Overall
 | Placebo | Exelon® greater than or equal to 6-12 mg/day | Placebo | Exelon® greater than or equal to 6-12 mg/day | Placebo | Exelon® greater than or equal to 6-12 mg/day
 | (n=868) | (n=1,189) | (n=788) | (n=987) | (n=868) | (n=1,189)
Event/% Discontinuing
Nausea | less than 1 | 8 | less than 1 | 1 | 1 | 8
Vomiting | less than 1 | 4 | less than 1 | 1 | less than 1 | 5
Anorexia | 0 | 2 | less than 1 | 1 | less than 1 | 3
Dizziness | less than 1 | 2 | less than 1 | 1 | less than 1 | 2

Most Frequent Adverse Clinical Events Seen in Association with the Use of Exelon

The most common adverse events, defined as those occurring at a frequency of at least 5% and twice the placebo rate, are largely predicted by Exelon's cholinergic effects. These include nausea, vomiting, anorexia, dyspepsia, and asthenia.

Gastrointestinal Adverse Reactions

Exelon use is associated with significant nausea, vomiting, and weight loss (see WARNINGS).

Adverse Events Reported in Controlled Trials

Table 2 lists treatment-emergent signs and symptoms that were reported in at least 2% of patients in placebo-controlled trials and for which the rate of occurrence was greater for patients treated with Exelon doses of 6-12 mg/day than for those treated with placebo. The prescriber should be aware that these figures cannot be used to predict the frequency of adverse events in the course of usual medical practice when patient characteristics and other factors may differ from those prevailing during clinical studies. Similarly, the cited frequencies cannot be directly compared with figures obtained from other clinical investigations involving different treatments, uses, or investigators. An inspection of these frequencies, however, does provide the prescriber with one basis by which to estimate the relative contribution of drug and non-drug factors to the adverse event incidences in the population studied.

In general, adverse reactions were less frequent later in the course of treatment.

No systematic effect of race or age could be determined from the incidence of adverse events in the controlled studies. Nausea, vomiting and weight loss were more frequent in women than men.

Table 2. Adverse Events Reported in Controlled Clinical Trials in at Least 2% of Patients Receiving Exelon® (6-12 mg/day) and at a Higher Frequency than Placebo-treated Patients
Body System/Adverse Event | Placebo (n=868) | Exelon® (6-12 mg/day) (n=1,189)
Percent of Patients with any Adverse Event | 79 | 92
Autonomic Nervous System
Sweating Increased | 1 | 4
Syncope | 2 | 3
Body as a Whole
Accidental Trauma | 9 | 10
Fatigue | 5 | 9
Asthenia | 2 | 6
Malaise | 2 | 5
Influenza-like Symptoms | 2 | 3
Weight Decrease | less than 1 | 3
Cardiovascular Disorders, General
Hypertension | 2 | 3
Central and Peripheral Nervous System
Dizziness | 11 | 21
Headache | 12 | 17
Somnolence | 3 | 5
Tremor | 1 | 4
Gastrointestinal System
Nausea | 12 | 47
Vomiting | 6 | 31
Diarrhea | 11 | 19
Anorexia | 3 | 17
Abdominal Pain | 6 | 13
Dyspepsia | 4 | 9
Constipation | 4 | 5
Flatulence | 2 | 4
Eructation | 1 | 2
Psychiatric Disorders
Insomnia | 7 | 9
Confusion | 7 | 8
Depression | 4 | 6
Anxiety | 3 | 5
Hallucination | 3 | 4
Aggressive Reaction | 2 | 3
Resistance Mechanism Disorders
Urinary Tract Infection | 6 | 7
Respiratory System
Rhinitis | 3 | 4

Other adverse events observed at a rate of 2% or more on Exelon 6-12 mg/day but at a greater or equal rate on placebo were chest pain, peripheral edema, vertigo, back pain, arthralgia, pain, bone fracture, agitation, nervousness, delusion, paranoid reaction, upper respiratory tract infection, infection (general), coughing, pharyngitis, bronchitis, rash (general), urinary incontinence.

Dementia Associated with Parkinson’s Disease Adverse Events Leading to Discontinuation

The rate of discontinuation due to adverse events in the single controlled trial of Exelon (rivastigmine tartrate) was 18.2% for patients receiving 3-12 mg/day compared to 11.2% for patients on placebo during the 24-week study.

The most frequent adverse events that led to discontinuation from this study, defined as those occurring in at least 1% of patients receiving Exelon and more frequent than those receiving placebo, were nausea (3.6% Exelon vs. 0.6% placebo), vomiting (1.9% Exelon vs. 0.6% placebo), and tremor (1.7% Exelon vs. 0.0% placebo).

Most Frequent Adverse Clinical Events Seen in Association with the Use of Exelon

The most common adverse events, defined as those occurring at a frequency of at least 5% and twice the placebo rate, are largely predicted by Exelon's cholinergic effects. These include nausea, vomiting, tremor, anorexia, and dizziness.

Adverse Events Reported in Controlled Trials

Table 3 lists treatment-emergent signs and symptoms that were reported in at least 2% of patients in placebo-controlled trials and for which the rate of occurrence was greater for patients treated with Exelon doses of 3-12 mg/day than for those treated with placebo. The prescriber should be aware that these figures cannot be used to predict the frequency of adverse events in the course of usual medical practice when patient characteristics and other factors may differ from those prevailing during clinical studies. Similarly, the cited frequencies cannot be directly compared with figures obtained from other clinical investigations involving different treatments, uses, or investigators. An inspection of these frequencies, however, does provide the prescriber with one basis by which to estimate the relative contribution of drug and non-drug factors to the adverse event incidences in the population studied.

In general, adverse reactions were less frequent later in the course of treatment.

Table 3. Adverse Events Reported in the Single Controlled Clinical Trial in at Least 2% of Patients Receiving Exelon® (3-12 mg/day) and at a Higher Frequency than Placebo-treated Patients
Body System/Adverse Event | Placebo (n=179) | Exelon® (3-12 mg/day) (n=362)
Percent of Patients with any Adverse Event | 71 | 84
Gastrointestinal Disorders
Nausea | 11 | 29
Vomiting | 2 | 17
Diarrhea | 4 | 7
Upper Abdominal Pain | 1 | 4
General Disorders and Administrative Site Conditions
Fatigue | 3 | 4
Asthenia | 1 | 2
Metabolism and Nutritional Disorders
Anorexia | 3 | 6
Dehydration | 1 | 2
Nervous System Disorders
Tremor | 4 | 10
Dizziness | 1 | 6
Headache | 3 | 4
Somnolence | 3 | 4
Parkinson’s Disease (worsening) | 1 | 3
Parkinsonism | 1 | 2
Psychiatric Disorders
Anxiety | 1 | 4
Insomnia | 2 | 3

Other Adverse Events Observed During Clinical Trials Dementia of the Alzheimer’s Type

Exelon has been administered to over 5,297 individuals during clinical trials worldwide. Of these, 4,326 patients have been treated for at least 3 months, 3,407 patients have been treated for at least 6 months, 2,150 patients have been treated for 1 year, 1,250 patients have been treated for 2 years, and 168 patients have been treated for over 3 years. With regard to exposure to the highest dose, 2,809 patients were exposed to doses of 10-12 mg, 2,615 patients treated for 3 months, 2,328 patients treated for 6 months, 1,378 patients treated for 1 year, 917 patients treated for 2 years, and 129 patients treated for over 3 years.

Treatment-emergent signs and symptoms that occurred during 8 controlled clinical trials and 9 open-label trials in North America, Western Europe, Australia, South Africa, and Japan were recorded as adverse events by the clinical investigators using terminology of their own choosing. To provide an overall estimate of the proportion of individuals having similar types of events, the events were grouped into a smaller number of standardized categories using a modified WHO dictionary, and event frequencies were calculated across all studies. These categories are used in the listing below. The frequencies represent the proportion of 5,297 patients from these trials who experienced that event while receiving Exelon. All adverse events occurring in at least 6 patients (approximately 0.1%) are included, except for those already listed elsewhere in labeling, WHO terms too general to be informative, relatively minor events, or events unlikely to be drug-caused. Events are classified by body system and listed using the following definitions: frequent adverse events – those occurring in at least 1/100 patients; infrequent adverse events – those occurring in 1/100 to 1/1,000 patients. These adverse events are not necessarily related to Exelon treatment and in most cases were observed at a similar frequency in placebo-treated patients in the controlled studies.

Autonomic Nervous System: Infrequent: Cold clammy skin, dry mouth, flushing, increased saliva.

Body as a Whole: Frequent: Accidental trauma, fever, edema, allergy, hot flushes, rigors. Infrequent: Edema periorbital or facial, hypothermia, edema, feeling cold, halitosis.

Cardiovascular System: Frequent: Hypotension, postural hypotension, cardiac failure.

Central and Peripheral Nervous System: Frequent: Abnormal gait, ataxia, paresthesia, convulsions. Infrequent: Paresis, apraxia, aphasia, dysphonia, hyperkinesia, hyperreflexia, hypertonia, hypoesthesia, hypokinesia, migraine, neuralgia, nystagmus, peripheral neuropathy.

Endocrine System: Infrequent: Goiter, hypothyroidism.

Gastrointestinal System: Frequent: Fecal incontinence, gastritis. Infrequent: Dysphagia, esophagitis, gastric ulcer, gastroesophageal reflux, GI hemorrhage, hernia, intestinal obstruction, melena, rectal hemorrhage, gastroenteritis, ulcerative stomatitis, duodenal ulcer, hematemesis, gingivitis, tenesmus, pancreatitis, colitis, glossitis.

Hearing and Vestibular Disorders: Frequent: Tinnitus.

Heart Rate and Rhythm Disorders: Frequent: Atrial fibrillation, bradycardia, palpitation. Infrequent: AV block, bundle branch block, sick sinus syndrome, cardiac arrest, supraventricular tachycardia, extrasystoles, tachycardia.

Liver and Biliary System Disorders: Infrequent: Abnormal hepatic function, cholecystitis.

Metabolic and Nutritional Disorders: Frequent: Dehydration, hypokalemia. Infrequent: Diabetes mellitus, gout, hypercholesterolemia, hyperlipemia, hypoglycemia, cachexia, thirst, hyperglycemia, hyponatremia.

Musculoskeletal Disorders: Frequent: Arthritis, leg cramps, myalgia. Infrequent: Cramps, hernia, muscle weakness.

Myo-, Endo-, Pericardial and Valve Disorders: Frequent: Angina pectoris, myocardial infarction.

Platelet, Bleeding, and Clotting Disorders: Frequent: Epistaxis. Infrequent: Hematoma, thrombocytopenia, purpura.

Psychiatric Disorders: Frequent: Paranoid reaction, confusion. Infrequent: Abnormal dreaming, amnesia, apathy, delirium, dementia, depersonalization, emotional lability, impaired concentration, decreased libido, personality disorder, suicide attempt, increased libido, neurosis, suicidal ideation, psychosis.

Red Blood Cell Disorders: Frequent: Anemia. Infrequent: Hypochromic anemia.

Reproductive Disorders (Female and Male): Infrequent: Breast pain, impotence, atrophic vaginitis.

Resistance Mechanism Disorders: Infrequent: Cellulitis, cystitis, herpes simplex, otitis media.

Respiratory System: Infrequent: Bronchospasm, laryngitis, apnea.

Skin and Appendages: Frequent: Rashes of various kinds (maculopapular, eczema, bullous, exfoliative, psoriaform, erythematous). Infrequent: Alopecia, skin ulceration, urticaria, contact dermatitis.

Special Senses: Infrequent: Perversion of taste, loss of taste.

Urinary System Disorders: Frequent: Hematuria. Infrequent: Albuminuria, oliguria, acute renal failure, dysuria, micturition urgency, nocturia, polyuria, renal calculus, urinary retention.

Vascular (extracardiac) Disorders: Infrequent: Hemorrhoids, peripheral ischemia, pulmonary embolism, thrombosis, deep thrombophlebitis, aneurysm, intracranial hemorrhage.

Vision Disorders: Frequent: Cataract. Infrequent: Conjunctival hemorrhage, blepharitis, diplopia, eye pain, glaucoma.

White Cell and Resistance Disorders: Infrequent: Lymphadenopathy, leukocytosis.

Dementia Associated with Parkinson’s Disease

Exelon has been administered to 485 individuals during clinical trials worldwide. Of these, 413 patients have been treated for at least 3 months, 253 patients have been treated for at least 6 months, and 113 patients have been treated for 1 year.

Additional treatment-emergent adverse events in patients with Parkinson’s disease dementia occurring in at least 1 patient (approximately 0.3%) are listed below, excluding events that are already listed above for the dementia of the Alzheimer’s type or elsewhere in labeling, WHO terms too general to be informative, relatively minor events, or events unlikely to be drug-caused. Events are classified by body system and listed using the following definitions: frequent adverse events – those occurring in at least 1/100 patients; infrequent adverse events – those occurring in 1/100 to 1/1,000 patients. These adverse events are not necessarily related to Exelon treatment and in most cases were observed at a similar frequency in placebo-treated patients in the controlled studies.

Cardiovascular System: Frequent: Chest pain. Infrequent: Sudden cardiac death.

Central and Peripheral Nervous System: Frequent: Dyskinesia, bradykinesia, restlessness, transient ischemic attack. Infrequent: Dystonia, hemiparesis, epilepsy, restless leg syndrome.

Endocrine System: Infrequent: Elevated prolactin level.

Gastrointestinal System: Frequent: Dyspepsia. Infrequent: Fecaloma, dysphagia, diverticulitis, peritonitis.

Hearing and Vestibular Disorders: Frequent: Vertigo. Infrequent: Meniere’s disease.

Heart Rate and Rhythm Disorders: Infrequent: Adam-Stokes syndrome.

Liver and Biliary System Disorders: Infrequent: Elevated alkaline phosphatase level, elevated gamma-glutamyltransferase level.

Musculoskeletal Disorders: Frequent: Back pain. Infrequent: Muscle stiffness, myoclonus, freezing phenomenon.

Psychiatric Disorders: Frequent: Agitation, depression. Infrequent: Delusion, insomnia.

Reproductive Disorders (Female and Male): Infrequent: endometrial hypertrophy, mastitis, prostatic adenoma.

Respiratory System: Frequent: Dyspnea. Infrequent: Cough.

Urinary System Disorders: Infrequent: Urinary incontinence, neurogenic bladder.

Vascular (extracardiac) Disorders: Infrequent: Vasovagal syncope, vasculitis.

Vision Disorders: Infrequent: Blurred vision, blepharospasm, conjunctivitis, retinopathy.

Post-Introduction Reports

Voluntary reports of adverse events temporally associated with Exelon that have been received since market introduction that are not listed above, and that may or may not be causally related to the drug include the following:

Skin and Appendages: Stevens-Johnson syndrome.

OVERDOSAGE

Because strategies for the management of overdose are continually evolving, it is advisable to contact a Poison Control Center to determine the latest recommendations for the management of an overdose of any drug.

As Exelon® (rivastigmine tartrate) has a short plasma half-life of about one hour and a moderate duration of acetylcholinesterase inhibition of 8-10 hours, it is recommended that in cases of asymptomatic overdoses, no further dose of Exelon should be administered for the next 24 hours.

As in any case of overdose, general supportive measures should be utilized. Overdosage with cholinesterase inhibitors can result in cholinergic crisis characterized by severe nausea, vomiting, salivation, sweating, bradycardia, hypotension, respiratory depression, collapse and convulsions. Increasing muscle weakness is a possibility and may result in death if respiratory muscles are involved. Atypical responses in blood pressure and heart rate have been reported with other drugs that increase cholinergic activity when coadministered with quaternary anticholinergics such as glycopyrrolate. Due to the short half-life of Exelon, dialysis (hemodialysis, peritoneal dialysis, or hemofiltration) would not be clinically indicated in the event of an overdose.

In overdoses accompanied by severe nausea and vomiting, the use of antiemetics should be considered. In a documented case of a 46-mg overdose with Exelon, the patient experienced vomiting, incontinence, hypertension, psychomotor retardation, and loss of consciousness. The patient fully recovered within 24 hours and conservative management was all that was required for treatment.

DOSAGE AND ADMINISTRATION

Dementia of the Alzheimer’s Type

The dosage of Exelon® (rivastigmine tartrate) shown to be effective in controlled clinical trials in Alzheimer’s disease is 6-12 mg/day, given as twice-a-day dosing (daily doses of 3 to 6 mg BID). There is evidence from the clinical trials that doses at the higher end of this range may be more beneficial.

The starting dose of Exelon is 1.5 mg twice a day (BID). If this dose is well tolerated, after a minimum of 2 weeks of treatment, the dose may be increased to 3 mg BID. Subsequent increases to 4.5 mg BID and 6 mg BID should be attempted after a minimum of 2 weeks at the previous dose. If adverse effects (e.g., nausea, vomiting, abdominal pain, loss of appetite) cause intolerance during treatment, the patient should be instructed to discontinue treatment for several doses and then restart at the same or next lower dose level. If treatment is interrupted for longer than several days, treatment should be reinitiated with the lowest daily dose and titrated as described above (see WARNINGS). The maximum dose is 6 mg BID (12 mg/day).

Dementia Associated with Parkinson’s Disease

The dosage of Exelon shown to be effective in the single controlled clinical trial conducted in dementia associated with Parkinson’s disease is 3-12 mg/day, given as twice-a-day dosing (daily doses of 1.5-6 mg BID). In that medical condition, the starting dose of Exelon is 1.5 mg BID; subsequently, the dose may be increased to 3 mg BID and further to 4.5 mg BID and 6 mg BID, based on tolerability, with a minimum of 4 weeks at each dose.

Exelon should be taken with meals in divided doses in the morning and evening.

Recommendations for Administration: Caregivers should be instructed in the correct procedure for administering Exelon Oral Solution. In addition, they should be directed to the Instruction Sheet (included with the product) describing how the solution is to be administered. Caregivers should direct questions about the administration of the solution to either their physician or pharmacist (see PRECAUTIONS: Information for Patients and Caregivers).

Patients should be instructed to remove the oral dosing syringe provided in its protective case, and using the provided syringe, withdraw the prescribed amount of Exelon Oral Solution from the container. Each dose of Exelon Oral Solution may be swallowed directly from the syringe or first mixed with a small glass of water, cold fruit juice or soda. Patients should be instructed to stir and drink the mixture.

Exelon Oral Solution and Exelon Capsules may be interchanged at equal doses.

HOW SUPPLIED

Exelon® (rivastigmine tartrate) Capsules equivalent to 1.5 mg, 3 mg, 4.5 mg, or 6 mg of rivastigmine base are available as follows:

1.5 mg Capsule – yellow, “Exelon 1,5 mg” is printed in red on the body of the capsule.

Bottles of 30………………………………………………...NDC 54868-4512-1

Bottles of 60..……………………………………………….NDC 54868-4512-0

3 mg Capsule – orange, “Exelon 3 mg” is printed in red on the body of the capsule.

Bottles of 60…………………………………………………NDC 54868-5839-0

4.5 mg Capsule – red, “Exelon 4,5 mg” is printed in white on the body of the capsule.

Bottles of 30………………………………………………..NDC 54868-5240-0

6 mg Capsule – orange and red, “Exelon 6 mg” is printed in red on the body of the capsule.

Bottles of 60…………………………………………………NDC 54868-5339-0

Store at 25°C (77°F); excursions permitted to 15-30°C (59-86°F) [see USP Controlled Room Temperature]. Store in a tight container.

REV: JUNE 2006 T2006-73

Distributed by:

Novartis Pharmaceuticals Corporation

East Hanover, New Jersey 07936

©Novartis

Repackaging and Relabeling by:
Physicians Total Care, Inc.
Tulsa, OK 74146

PRINCIPAL DISPLAY PANEL

Exelon® (rivastigmine tartrate) Capsules

equivalent to

1.5 mg

Exelon® (rivastigmine tartrate) Capsules

equivalent to

3 mg

Exelon® (rivastigmine tartrate) Capsules

equivalent to

4.5 mg

Exelon® (rivastigmine tartrate) Capsules

equivalent to

6 mg